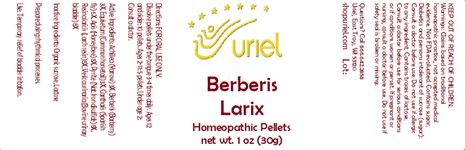 DRUG LABEL: Berberis Larix
NDC: 48951-2157 | Form: PELLET
Manufacturer: Uriel Pharmacy Inc
Category: homeopathic | Type: HUMAN OTC DRUG LABEL
Date: 20241217

ACTIVE INGREDIENTS: ACHILLEA MILLEFOLIUM 3 [hp_X]/1 1; BERBERIS VULGARIS ROOT BARK 3 [hp_X]/1 1; EQUISETUM ARVENSE TOP 3 [hp_X]/1 1; LYTTA VESICATORIA 6 [hp_X]/1 1; APIS MELLIFERA 8 [hp_X]/1 1; LARIX DECIDUA RESIN 8 [hp_X]/1 1; SUS SCROFA URINARY BLADDER 8 [hp_X]/1 1; FERROUS DISULFIDE 8 [hp_X]/1 1
INACTIVE INGREDIENTS: SUCROSE; LACTOSE, UNSPECIFIED FORM

Berberis Larix

INDICATIONS AND USAGE

Directions: FOR ORAL USE ONLY.

DOSAGE AND ADMINISTRATION

Dissolve pellets under the tongue 3-4 times daily. Ages 12 and older: 10 pellets. Ages 2-11: 5 pellets. Under age 2: Consult a doctor.

ACTIVE INGREDIENT

Active Ingredients: Achillea (Yarrow) 3X, Berberis (Barberry) 3X, Equisetum (Common horsetail) 3X, Cantharis (Spanish fly) 6X, Apis (Honeybee) 8X, Pyrite (Nat. Iron disulfide) 8X, Resina laricis (Larch resin) 8X, Vesica urinaria (Bovine urinary bladder) 8X

Inactive Ingredients: Organic sucrose, Lactose

Prepared using rhythmical processes.

PURPOSE

Use: Temporary relief of bladder irritation.

KEEP OUT OF REACH OF CHILDREN.

WARNINGS

Warnings: Claims based on traditional homeopathic practice, not accepted medical evidence. Not FDA evaluated. Contains sugar. Diabetics and persons intolerant of sucrose (sugar): Consult a doctor before use. Contains traces of lactose. Do not use if allergic to any ingredient. Consult a doctor before use for serious conditions or if conditions worsen or persist. If pregnant or nursing, consult a doctor before use. Do not use if safety seal is broken or missing.

Questions? Call 866.642.2858
Uriel, East Troy, WI 53120
shopuriel.com Lot: